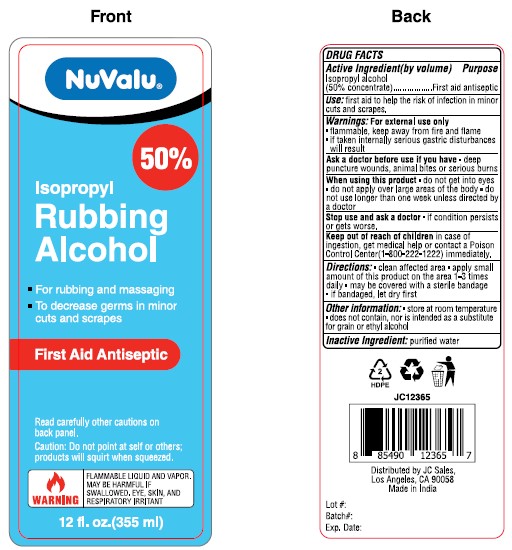 DRUG LABEL: ISOPROPYL RUBBING ALCOHOL 50 PERCENT
NDC: 72520-315 | Form: SOLUTION
Manufacturer: JC SALES
Category: otc | Type: HUMAN OTC DRUG LABEL
Date: 20251210

ACTIVE INGREDIENTS: ISOPROPYL ALCOHOL 50 mL/100 mL
INACTIVE INGREDIENTS: WATER

JC Sales (as PLD) - NuValu ISOPROPYL RUBBING ALCOHOL, 50% (72520-315)

Active ingredient

ISOPROPYL ALCOHOL 50%

Purpose

FIRST AID ANTISEPTIC

Uses

FIRST AID TO HELP THE RISK OF INFECTION IN MINOR CUTS AND SCRAPES.

WARNINGS

For external use only.

- FLAMMABLE, KEEP AWAY FROM FIRE OR FLAME
- IF TAKEN INTERNALLY SERIOUS GASTRIC DISTURBANCES WILL RESULT

ASK A DOCTOR BEFORE USE IF YOU HAVE

- DEEP PUNCTURE WOUNDS, ANIMAL BITES OR SERIOUS BURNS

WHEN USING THIS PRODUCT

- DO NOT GET INTO EYES
- DO NOT APPLY OVER LARGE AREAS OF THE BODY.
- DO NOT USE LONGER THAN ONE WEEK UNLESS DIRECTED BY A DOCTOR.

STOP USE AND ASK A DOCTOR IF

- CONDITION PERSISTS OR GET WORSE.

KEEP OUT OF REACH OF CHILDREN. IN CASE OF INGESTION, GET MEDICAL HELP OR CONTRACT A POISON CONTROL CENTER (1-800-222-1222) IMMEDIATELY.

Directions

- CLEAN THE AFFECTED AREA.
- APPLY A SMALL AMOUNT OF THIS PRODUCT ON THE AREA 1 TO 3 TIMES DAILY
- MAY BE COVERED WITH A STERILE BANDAGE
- IF BANDAGED, LET DRY FIRST.

OTHER INFORMATION

- STORE AT ROOM TEMPERATURE
- DOES NOT CONTAIN, NOR IS INTENDED AS A SUBSTITUTE FOR GRAIN OR ETHYL ALCOHOL

Inactive Ingredient

PURIFIED WATER